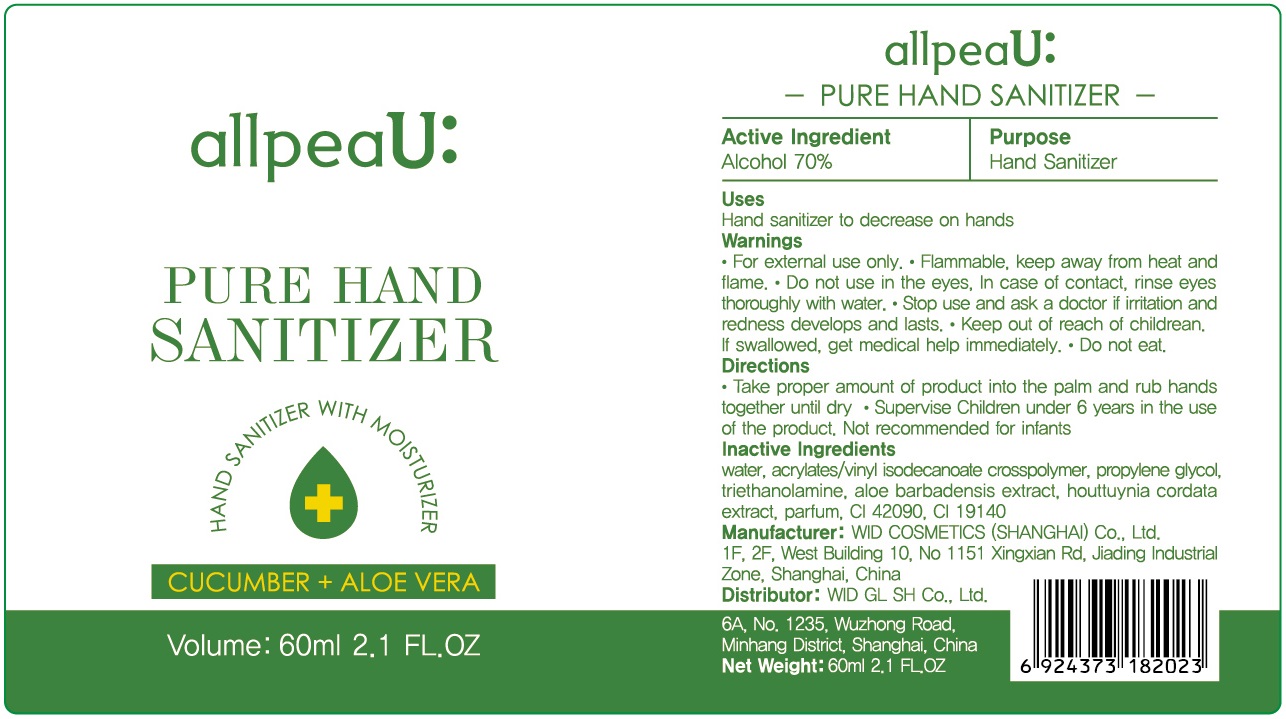 DRUG LABEL: allpeaU Pure Hand Sanitizer
NDC: 75567-1011 | Form: GEL
Manufacturer: WID Cosmetics (Shanghai) Co., Ltd.
Category: otc | Type: HUMAN OTC DRUG LABEL
Date: 20200427

ACTIVE INGREDIENTS: ALCOHOL 42 mL/60 mL
INACTIVE INGREDIENTS: HOUTTUYNIA CORDATA FLOWERING TOP; FD&C BLUE NO. 1; CUCUMBER; TROLAMINE; WATER; PROPYLENE GLYCOL; BUTYL ACRYLATE/METHYL METHACRYLATE/METHACRYLIC ACID COPOLYMER (18000 MW); ALOE VERA LEAF; FD&C YELLOW NO. 5

WID, Hand Sanitizer, 70% Alcohol, Gel, 60mL

Active Ingredient(s)

Alcohol 75% v/v. Purpose: Hand Sanitizer

Purpose

Hand Sanitizer

Use

Hand sanitizer to decrease on hands.

Warnings

- For external use only.
- Flammable. Keep away from heat and flame.

Do not use in the eyes. In case of contact, rinse eyes thoroughly with water.

When using this product do not use in or near the eyes.

In case of contact, rinse eyes thoroughly with water.

Stop use and ask a doctor if irritation and redness develops and lasts.

Keep out of reach of children. If swallowed, get medical help immediately.

Directions

- Take proper amount of product into the palm and rub hands together until dry.
- Supervise children under 6 years in the use of the product. Not recommended for infants.

Other information

Store below 110℉ (43℃).

May discolor certain fabrics or surfaces.

Inactive ingredients

water, acrylates/vinyl isodecanoate crosspolymer, propylene glycol, triethanolamine, aloe barbadensis extract, cucumis sativus extract, houttuynia cordata extract, parfum, CI 42090, CI 19140